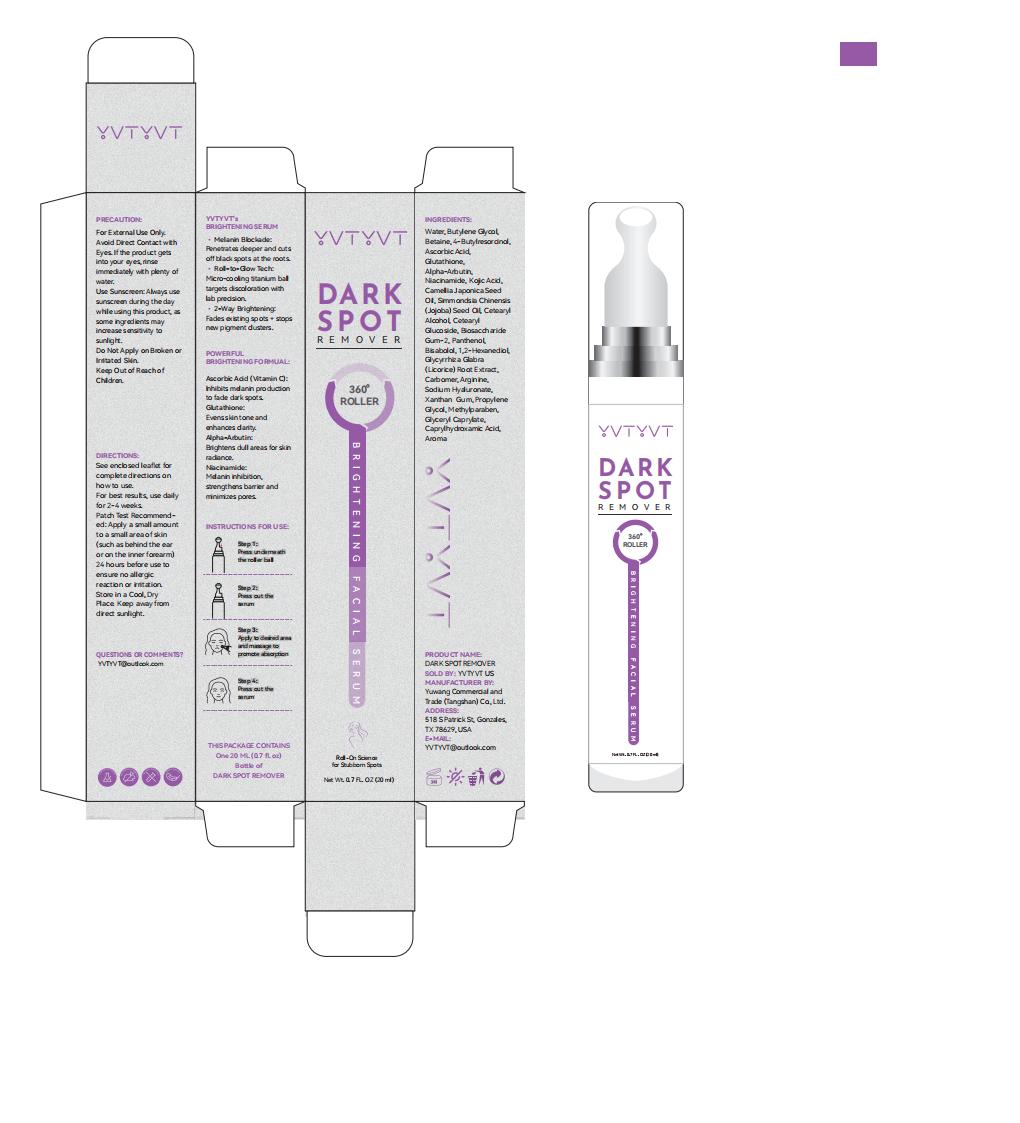 DRUG LABEL: YVTYVT DARK SPOT
NDC: 85212-0040 | Form: LOTION
Manufacturer: Beijing JUNGE Technology Co., Ltd.
Category: otc | Type: HUMAN OTC DRUG LABEL
Date: 20250515

ACTIVE INGREDIENTS: KOJIC ACID 1 g/100 mL; ASCORBIC ACID 2 g/100 mL
INACTIVE INGREDIENTS: SODIUM HYALURONATE 0.5 mL/100 mL; PROPYLENE GLYCOL 2-HEXANOATE 0.1 mL/100 mL; BIOSACCHARIDE GUM-2 1 mL/100 mL; WATER 78.6 mL/100 mL; BISABOLOL 0.5 mL/100 mL; 4-BUTYLRESORCINOL 2 mL/100 mL; CETEARYL GLUCOSIDE 1 mL/100 mL; 1,2-HEXANEDIOL 0.5 mL/100 mL; CAMELLIA JAPONICA SEED OIL 1 mL/100 mL; NIACINAMIDE 1 mL/100 mL; BUTYLENE GLYCOL 5 mL/100 mL; CETEARYL ALCOHOL 1 mL/100 mL; BETAINE 2 mL/100 mL; XANTHAN GUM 0.1 mL/100 mL; SIMMONDSIA CHINENSIS (JOJOBA) SEED OIL 1 mL/100 mL; GLUTATHIONE 1 mL/100 mL; GLYCERYL CAPRYLATE 0.1 mL/100 mL; METHYLPARABEN 0.1 mL/100 mL; PANTHENOL 0.5 mL/100 mL

ALARMS

For External Use Only.
Avoid Direct Contact with Eyes. If the product gets into your eyes, rinse immediately with plenty of water.
Discontinue Use if Irritation Occurs: If redness, itching, or irritation develops, stop use and consult a dermatologist.
Use Sunscreen: Always use sunscreen during the day while using this product, as some ingredients may increase sensitivity to sunlight.
Do Not Apply on Broken or Irritated Skin.
Keep Out of Reach of Children.

INACTIVE INGREDIENT

WATER
BUTYLENE GLYCOL
BETAINE
4-BUTYLRESORCINOL
GLUTATHIONE
NIACINAMIDE
CAMELLIA JAPONICA SEED OIL
SIMMONDSIA CHINENSIS (JOJOBA) SEED OIL
CETEARYL ALCOHOL
CETEARYL GLUCOSIDE
BIOSACCHARIDE GUM-2
PANTHENOL
BISABOLOL
1,2-HEXANEDIOL
SODIUM HYALURONATE
XANTHAN GUM
PROPYLENE GLYCOL
METHYLPARABEN
GLYCERYL CAPRYLATE

DOSAGE AND ADMINISTRATION

For best results, use daily for 2-4 weeks

WHEN USING

Step 1: Cleanse skin to remove impurities.
Step 2: Apply appropriate amount post - cleansing.
Step 3: Use before heavy moisturizers or oils for better absorption.

STOP USE

If the product gets into your eyes, rinse immediately with plenty of water.
Discontinue Use if Irritation Occurs: If redness, itching, or irritation develops, stop use and consult a dermatologist.

Do Not Apply on Broken or Irritated Skin.

ACTIVE INGREDIENT

ASCORBIC ACID, KOJIC ACID

WARNINGS

For External Use Only.
Avoid Direct Contact with Eyes.
If the product gets into your eyes, rinse immediately with plenty of water.
Discontinue Use if Irritation Occurs: If redness, itching, or irritation develops, stop use and consult a dermatologist.
Do Not Apply on Broken or Irritated Skin. Keep Out of Reach of Children.

INDICATIONS AND USAGE

Used to remove dark spots
Reduce pigmentation
For skin moisturizing

PURPOSE

Used to remove dark spots